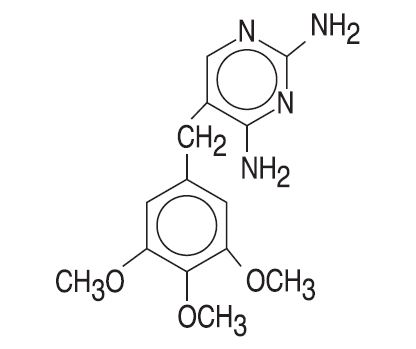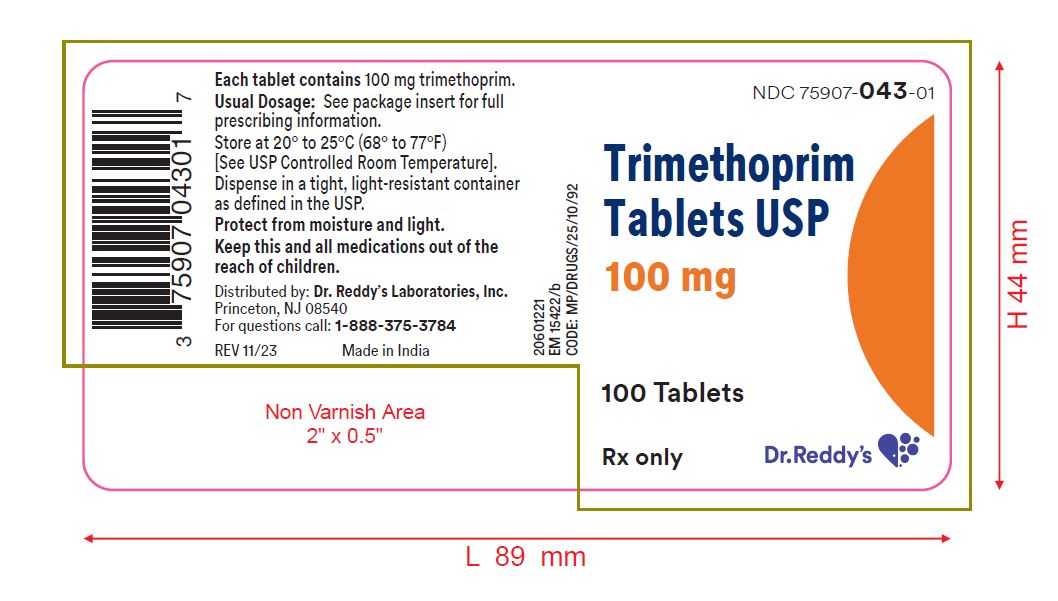 DRUG LABEL: Trimethoprim
NDC: 75907-043 | Form: TABLET
Manufacturer: Dr. Reddy's Labratories Inc.
Category: prescription | Type: HUMAN PRESCRIPTION DRUG LABEL
Date: 20240126

ACTIVE INGREDIENTS: TRIMETHOPRIM 100 mg/1 1
INACTIVE INGREDIENTS: SILICON DIOXIDE; DIBASIC CALCIUM PHOSPHATE DIHYDRATE; MAGNESIUM STEARATE; MICROCRYSTALLINE CELLULOSE; STARCH, CORN; SODIUM STARCH GLYCOLATE TYPE A POTATO

TRIMETHOPRIM TABLETS, USP
Rx only

To reduce the development of drug-resistant bacteria and maintain the effectiveness of trimethoprim tablets, USP and other antibacterial drugs, trimethoprim tablets, USP should be used only to treat or prevent infections that are proven or strongly suspected to be caused by bacteria.

DESCRIPTION

Trimethoprim is a synthetic antibacterial available in tablet form for oral administration. Each scored white tablet contains 100 mg trimethoprim.

Trimethoprim is 5-[(3,4,5-trimethoxyphenyl)methyl]-2,4-pyrimidinediamine. It is a white to light yellow, odorless, bitter compound with a molecular weight of 290.32 and the molecular formula C14H18N4O3. The structural formula is:

Inactive Ingredients

Colloidal silicon dioxide, dibasic calcium phosphate dihydrate, magnesium stearate, microcrystalline cellulose, pregelatinized starch, and sodium starch glycolate.

CLINICAL PHARMACOLOGY

Trimethoprim is rapidly absorbed following oral administration. It exists in the blood as unbound, protein-bound, and metabolized forms. Ten to twenty percent of trimethoprim is metabolized, primarily in the liver; the remainder is excreted unchanged in the urine. The principal metabolites of trimethoprim are the 1- and 3-oxides and the 3'- and 4'-hydroxy derivatives. The free form is considered to be the therapeutically active form. Approximately 44% of trimethoprim is bound to plasma proteins.

Mean peak serum concentrations of approximately 1.0 mcg/mL occur 1 to 4 hours after oral administration of a single 100 mg dose. A single 200 mg dose will result in serum levels approximately twice as high. The half-life of trimethoprim ranges from 8 to 10 hours. However, patients with severely impaired renal function exhibit an increase in the half-life of trimethoprim, which requires either dosage regimen adjustment or not using the drug in such patients (see DOSAGE AND ADMINISTRATION). During a 13 week study of trimethoprim administered at a daily dosage of 200 mg (50 mg q.i.d.), the mean minimum steady-state concentration of the drug was 1.1 mcg/mL. Steady-state concentrations were achieved within 2 to 3 days of chronic administration and were maintained throughout the experimental period.

Excretion of trimethoprim is primarily by the kidneys through glomerular filtration and tubular secretion. Urine concentrations of trimethoprim are considerably higher than are the concentrations in the blood. After a single oral dose of 100 mg, urine concentrations of trimethoprim ranged from 30 to 160 mcg/mL during the 0 to 4 hour period and declined to approximately 18 to 91 mcg/mL during the 8 to 24 hour period. A 200 mg single oral dose will result in trimethoprim urine levels approximately twice as high. After oral administration, 50% to 60% of trimethoprim is excreted in the urine within 24 hours, approximately 80% of this being unmetabolized trimethoprim.

Since normal vaginal and fecal flora are the source of most pathogens causing urinary tract infections, it is relevant to consider the distribution of trimethoprim into these sites. Concentrations of trimethoprim in vaginal secretions are consistently greater than those found simultaneously in the serum, being typically 1.6 times the concentrations of simultaneously obtained serum samples. Sufficient trimethoprim is excreted in the feces to markedly reduce or eliminate trimethoprim-susceptible organisms from the fecal flora.

Trimethoprim also passes the placental barrier and is excreted in human milk.

Microbiology

Mechanism of Action

Trimethoprim blocks the production of tetrahydrofolic acid from dihydrofolic acid by binding to and reversibly inhibiting the required enzyme, dihydrofolate reductase. This binding is very much stronger for the bacterial enzyme than for the corresponding mammalian enzyme. Thus, trimethoprim selectively interferes with bacterial biosynthesis of nucleic acids and proteins.

Resistance

Resistance to trimethoprim may be conferred by a variety of mechanisms including cell wall impermeability, overproduction of the chromosomal dihydrofolate reductase (DHFR) enzyme, production of a resistant chromosomal DHFR enzyme or production of a plasmid-mediated trimethoprim-resistant DHFR enzyme. Acinetobacter baumannii/Acinetobacter calcoaceticus complex, Burkholderia cepacia complex, Pseudomonas aeruginosa, Stenotrophomonas maltophilia are intrinsically resistant to trimethoprim. Non-Enterobacteriaceae fecal organisms, Bacteroides spp. and Lactobacillus spp. are not susceptible to trimethoprim at the concentrations obtained with the recommended dosage. Enterococcus spp, (E. faecalis, E. faecium, E. gallinarum/E. casseliflavus) may appear active in vitro to trimethoprim but are not effective clinically and should not be reported as susceptible. Moraxella catarrhalis isolates were found consistently resistant to trimethoprim.

Antimicrobial Activity

Trimethoprim has been shown to be active against most strains of the following microorganisms, both in vitro and in clinical infections as described in the INDICATIONS AND USAGE section.

Aerobic gram-positive bacteria

Staphylococcus species (coagulase-negative strains, including S. saprophyticus)

Aerobic gram-negative bacteria

Enterobacter species

Escherichia coli

Klebsiella pneumoniae

Proteus mirabilis

Susceptibility Test Methods

For specific information regarding susceptibility test interpretive criteria, and associated test methods and quality control standards recognized by FDA for this drug, please see: http://www.fda.gov/STIC.

INDICATIONS AND USAGE

To reduce the development of drug-resistant bacteria and maintain the effectiveness of trimethoprim tablets, USP and other antibacterial drugs, trimethoprim tablets, USP should be used only to treat or prevent infections that are proven or strongly suspected to be caused by susceptible bacteria. When culture and susceptibility information are available, they should be considered in selecting or modifying antibacterial therapy. In the absence of such data, local epidemiology and susceptibility patterns may contribute to the empiric selection of therapy.

For the treatment of initial episodes of uncomplicated urinary tract infections due to susceptible strains of the following organisms: Escherichia coli, Proteus mirabilis, Klebsiella pneumoniae, Enterobacter species, and coagulase-negative Staphylococcus species, including S. saprophyticus.

Cultures and susceptibility tests should be performed to determine the susceptibility of the bacteria to trimethoprim. Therapy may be initiated prior to obtaining the results of these tests.

CONTRAINDICATIONS

Trimethoprim is contraindicated in individuals hypersensitive to trimethoprim and in those with documented megaloblastic anemia due to folate deficiency.

WARNINGS

Serious hypersensitivity reactions have been reported rarely in patients on trimethoprim therapy. Trimethoprim has been reported rarely to interfere with hematopoiesis, especially when administered in large doses and/or for prolonged periods.

The presence of clinical signs such as sore throat, fever, pallor, or purpura may be early indications of serious blood disorders (see OVERDOSAGE, Chronic).

Complete blood counts should be obtained if any of these signs are noted in a patient receiving trimethoprim and the drug discontinued if a significant reduction in the count of any formed blood element is found.

Clostridium difficile associated diarrhea (CDAD) has been reported with use of nearly all antibacterial agents, including trimethoprim tablets, USP, and may range in severity from mild diarrhea to fatal colitis. Treatment with antibacterial agents alters the normal flora of the colon leading to overgrowth of C. difficile.

C. difficile produces toxins A and B which contribute to the development of CDAD. Hypertoxin producing strains of C. difficile cause increased morbidity and mortality, as these infections can be refractory to antimicrobial therapy and may require colectomy. CDAD must be considered in all patients who present with diarrhea following antibiotic use. Careful medical history is necessary since CDAD has been reported to occur over two months after the administration of antibacterial agents.

If CDAD is suspected or confirmed, ongoing antiobiotic use not directed against C. difficile may need to be discontinued. Appropriate fluid and electrolyte management, protein supplementation, antibiotic treatment of C. difficile, and surgical evaluation should be instituted as clinically indicated.

PRECAUTIONS

General

Prescribing trimethoprim tablets, USP in the absence of a proven or strongly suspected bacterial infection or a prophylactic indication is unlikely to provide benefit to the patient and increases the risk of the development of drug-resistant bacteria.

Trimethoprim should be given with caution to patients with possible folate deficiency. Folates may be administered concomitantly without interfering with the antibacterial action of trimethoprim. Trimethoprim should also be given with caution to patients with impaired renal or hepatic function (see CLINICAL PHARMACOLOGY and DOSAGE AND ADMINISTRATION).

Information for Patients

Patients should be counseled that antibacterial drugs including trimethoprim tablets, USP should only be used to treat bacterial infections. They do not treat viral infections (e.g., the common cold). When trimethoprim tablets, USP are prescribed to treat a bacterial infection, patients should be told that although it is common to feel better early in the course of therapy, the medication should be taken exactly as directed. Skipping doses or not completing the full course of therapy may (1) decrease the effectiveness of the immediate treatment and (2) increase the likelihood that bacteria will develop resistance and will not be treatable by trimethoprim tablets, USP or other antibacterial drugs in the future.

Diarrhea is a common problem caused by antibiotics which usually ends when the antibiotic is discontinued. Sometimes after starting treatment with antibiotics, patients can develop watery and bloody stools (with and without stomach cramps and fever) even as late as two or more months after having taken the last dose of the antibiotic. If this occurs, patients should contact their physician as soon as possible.

Drug Interactions

Trimethoprim may inhibit the hepatic metabolism of phenytoin. Trimethoprim, given at a common clinical dosage, increased the phenytoin half-life by 51% and decreased the phenytoin metabolic clearance rate by 30%. When administering these drugs concurrently, one should be alert for possible excessive phenytoin effect.

Drug/Laboratory Test Interactions

Trimethoprim can interfere with a serum methotrexate assay as determined by the Competitive Binding Protein Technique (CBPA) when a bacterial dihydrofolate reductase is used as the binding protein. No interference occurs, however, if methotrexate is measured by a radioimmunoassay (RIA).

The presence of trimethoprim may also interfere with the Jaffé alkaline picrate reaction assay for creatinine, resulting in overestimations of about 10% in the range of normal values.

Carcinogenesis, Mutagenesis, Impairment of Fertility

Carcinogenesis

Long-term studies in animals to evaluate carcinogenic potential have not been conducted with trimethoprim.

Mutagenesis

Trimethoprim was demonstrated to be nonmutagenic in the Ames assay. In studies at two laboratories, no chromosomal damage was detected in cultured Chinese hamster ovary cells at concentrations approximately 500 times human plasma levels; at concentrations approximately 1000 times human plasma levels in these same cells, a low level of chromosomal damage was induced at one of the laboratories. No chromosomal abnormalities were observed in cultured human leukocytes at concentrations of trimethoprim up to 20 times human steady-state plasma levels. No chromosomal effects were detected in peripheral lymphocytes of human subjects receiving 320 mg of trimethoprim in combination with up to 1600 mg of sulfamethoxazole per day for as long as 112 weeks.

Impairment of Fertility

No adverse effects on fertility or general reproductive performance were observed in rats given trimethoprim in oral dosages as high as 70 mg/kg/day for males and 14 mg/kg/day for females.

Pregnancy

Teratogenic Effects

Trimethoprim has been shown to be teratogenic in the rat when given in doses 40 times the human dose. In some rabbit studies, the overall increase in fetal loss (dead and resorbed and malformed conceptuses) was associated with doses six times the human therapeutic dose.

While there are no large, well-controlled studies on the use of trimethoprim in pregnant women, Brumfitt and Pursell,^1 in a retrospective study, reported the outcome of 186 pregnancies during which the mother received either placebo or trimethoprim in combination with sulfamethoxazole. The incidence of congenital abnormalities was 4.5% (3 of 66) in those who received placebo and 3.3% (4 of 120) in those receiving trimethoprim and sulfamethoxazole. There were no abnormalities in the 10 children whose mothers received the drug during the first trimester. In a separate survey, Brumfitt and Pursell also found no congenital abnormalities in 35 children whose mothers had received trimethoprim and sulfamethoxazole at the time of conception or shortly thereafter.

Because trimethoprim may interfere with folic acid metabolism, trimethoprim should be used during pregnancy only if the potential benefit justifies the potential risk to the fetus.

Nonteratogenic Effects

The oral administration of trimethoprim to rats at a dose of 70 mg/kg/day commencing with the last third of gestation and continuing through parturition and lactation caused no deleterious effects on gestation or pup growth and survival.

Nursing Mothers

Trimethoprim is excreted in human milk. Because trimethoprim may interfere with folic acid metabolism, caution should be exercised when trimethoprim is administered to a nursing woman.

Pediatric Use

Safety and effectiveness in pediatric patients below the age of 2 months have not been established. The effectiveness of trimethoprim as a single agent has not been established in pediatric patients under 12 years of age.

Geriatric Use

Clinical studies of trimethoprim tablets did not include sufficient numbers of subjects aged 65 and over to determine whether they respond differently from younger subjects. Other reported clinical experience^2,3 has not identified differences in response between the elderly and younger patients. In general, dose selection for an elderly patient should be cautious, usually starting at the low end of the dosing range, reflecting the greater frequency of decreased hepatic, renal or cardiac function, and of concomitant disease or other drug therapy.

Case reports of hyperkalemia in elderly patients receiving trimethoprim-sulfamethoxazole have been published.^4 Trimethoprim is known to be substantially excreted by the kidney, and the risk of toxic reactions to this drug may be greater in patients with impaired renal function. Because elderly patients are more likely to have decreased renal function, care should be taken in dose selection, and it may be useful to monitor potassium concentrations and to monitor renal function by calculating creatinine clearance.

ADVERSE REACTIONS

The adverse effects encountered most often with trimethoprim were rash and pruritus.

To report SUSPECTED ADVERSE EVENTS, contact Dr. Reddy’s Laboratories Inc, at 1-888-375-3784 or FDA at 1-800-FDA-1088 or http://www.fda.gov/medwatch for voluntary reporting of adverse reactions.

Dermatologic

Rash, pruritus, and phototoxic skin eruptions. At the recommended dosage regimens of 100 mg b.i.d. or 200 mg q.d., each for 10 days, the incidence of rash is 2.9% to 6.7%. In clinical studies which employed high doses of trimethoprim, an elevated incidence of rash was noted. These rashes were maculopapular, morbilliform, pruritic, and generally mild to moderate, appearing 7 to 14 days after the initiation of therapy.

Hypersensitivity

Rare reports of exfoliative dermatitis, erythema multiforme, Stevens-Johnson syndrome, toxic epidermal necrolysis (Lyell Syndrome), and anaphylaxis have been received.

Gastrointestinal

Epigastric distress, nausea, vomiting, and glossitis. Elevation of serum transaminase and bilirubin has been noted, but the significance of this finding is unknown. Cholestatic jaundice has been rarely reported.

Hematologic

Thrombocytopenia, leukopenia, neutropenia, megaloblastic anemia, and methemoglobinemia.

Metabolic

Hyperkalemia, hyponatremia.

Neurologic

Aseptic meningitis has been rarely reported.

Miscellaneous

Fever, and increases in BUN and serum creatinine levels.

OVERDOSAGE

Acute

Signs of acute overdosage with trimethoprim may appear following ingestion of 1 gram or more of the drug and include nausea, vomiting, dizziness, headaches, mental depression, confusion, and bone marrow depression (see Chronic subsection).

Treatment consists of gastric lavage and general supportive measures. Acidification of the urine will increase renal elimination of trimethoprim. Peritoneal dialysis is not effective and hemodialysis is only moderately effective in eliminating the drug.

Chronic

Use of trimethoprim at high doses and/or for extended periods of time may cause bone marrow depression manifested as thrombocytopenia, leukopenia, and/or megaloblastic anemia. If signs of bone marrow depression occur, trimethoprim should be discontinued and the patient should be given leucovorin; 5 to 15 mg leucovorin daily has been recommended by some investigators.

DOSAGE AND ADMINISTRATION

The usual oral adult dosage is 100 mg of trimethoprim every 12 hours or 200 mg of trimethoprim every 24 hours, each for 10 days. The use of trimethoprim in patients with a creatinine clearance of less than 15 mL/min is not recommended. For patients with a creatinine clearance of 15 to 30 mL/min, the dose should be 50 mg every 12 hours.

HOW SUPPLIED

Trimethoprim tablets, USP, 100 mg: White, round, convex tablet, debossed "9", scored, "3" on one side and debossed "21 58" on the other, in bottles of 100. NDC 75907-043-01

Store at 20° to 25°C (68° to 77°F) [See USP Controlled Room Temperature].

Dispense in a tight, light-resistant container as defined in the USP.

REFERENCES

1. Brumfitt W, Pursell R. Trimethoprim-sulfamethoxazole in the treatment of bacteriuria in women. J Infect Dis. 1973;128(suppl): S657-S663.
2. Lacey RW, Simpson MHC, Fawcett C, et al. Comparison of single-dose trimethoprim with a five-day course for the treatment of urinary tract infections in the elderly. Age and Ageing 10: 179-185, 1981.
3. Ewer TC, Bailey RR, Gilchrist NL, et al. Comparative study of norfloxacin and trimethoprim for the treatment of elderly patients with urinary tract infection. NZ Med J 101: 537-539, 1988.
4. Marinella MA. Trimethoprim-induced hyperkalemia: An analysis of reported cases. Gerontology 45: 209-212, 1999.

Distributed by:
Dr. Reddy’s Laboratories Inc.
Princeton, NJ 08540
Made in India

Rev. 11/2023

PRINCIPAL DISPLAY PANEL - 100 mg Tablet Bottle Label

NDC 75907-043-01

Trimethoprim
Tablets USP

100 mg

Rx Only

100 Tablets

Dr. Reddy's Laboratories, Inc.